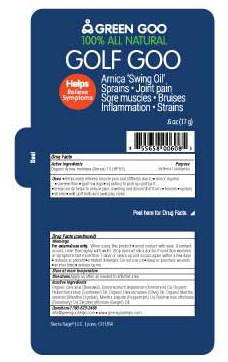 DRUG LABEL: Golf Goo
NDC: 70994-201 | Form: SALVE
Manufacturer: Sierra Sage Herbs LLC
Category: homeopathic | Type: HUMAN OTC DRUG LABEL
Date: 20170208

ACTIVE INGREDIENTS: ARNICA MONTANA FLOWER 1 [hp_X]/17 g
INACTIVE INGREDIENTS: OLIVE OIL; YELLOW WAX; SUNFLOWER OIL; MENTHOL; ROSEMARY OIL; CINNAMON OIL; GINGER OIL; MENTHA PIPERITA

Golf Goo

OTC Purpose Golf Goo

External Analgesic

OTC Active Ingredients

Organic Arnica montana (Arnica) 1X (HPUS)

Indications & Usage

• temporarily relieves muscle pain & stiffness due to • minor injuries • overexertion • long days of golfing
• temporarily helps to soothe pain, swelling & discoloration from • bruises • sprains • strains
• provides symptomatic relief of pain associated with osteoarthritis in joints

Warnings

Warnings For external use only.
-Don’t use on damaged or broken skin.
-When using this product keep out of eyes. Rinse with water to remove.
-Stop using and ask a doctor if rash or irritation occurs.

Keep Out of Reach of Children

Storage and Handling

Store at room temperature.

Dosage & Administration

Apply as often as needed to affected area.

Inactive Ingredients

Organic Cera alba (Beeswax), Cinnamomum zeylanicum (Cinnamon) Oil, Organic Helianthus annus (Sunflower) Oil, Organic Olea europaea (Olive) Oil, Organic Mentha arvensis (Menthol Crystals), Mentha piperita (Peppermint) Oil, Rosmarinus officinalis (Rosemary) Oil, Zingiber officinale (Ginger) Oil.